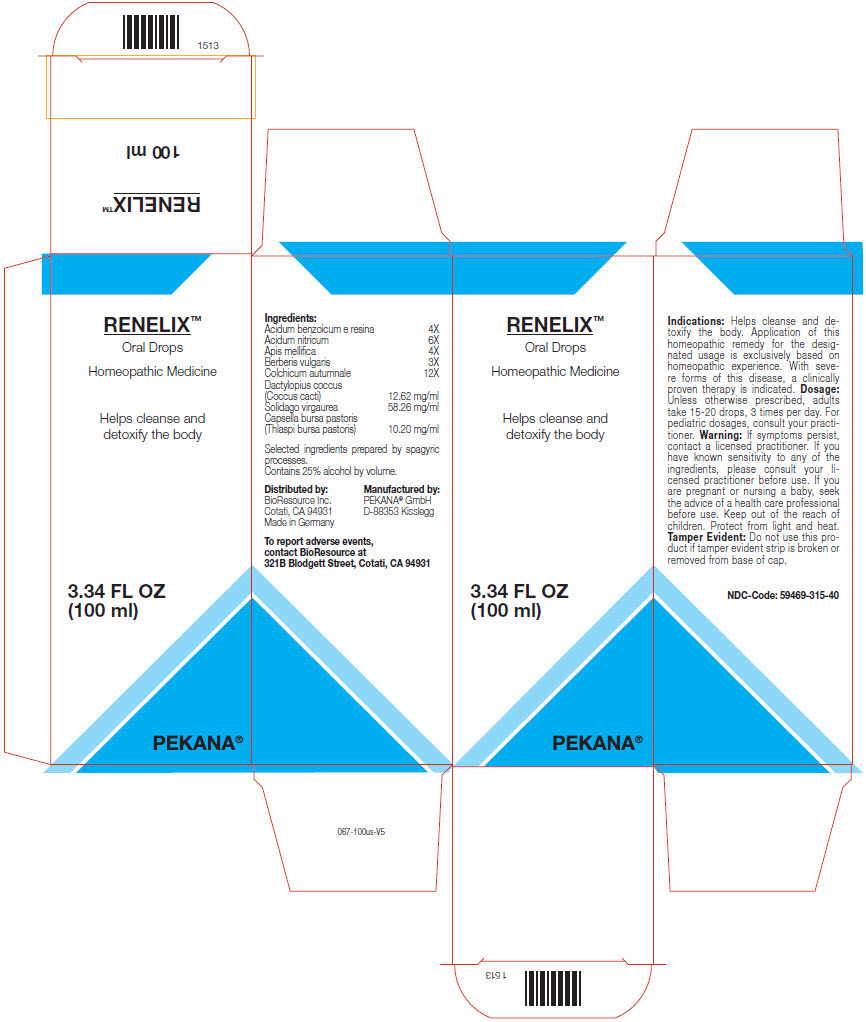 DRUG LABEL: RENELIX
NDC: 59469-315 | Form: SOLUTION/ DROPS
Manufacturer: PEKANA Naturheilmittel GmbH
Category: homeopathic | Type: HUMAN OTC DRUG LABEL
Date: 20230111

ACTIVE INGREDIENTS: BENZOIC ACID 4 [hp_X]/50 mL; NITRIC ACID 6 [hp_X]/50 mL; APIS MELLIFERA 4 [hp_X]/50 mL; BERBERIS VULGARIS ROOT BARK 3 [hp_X]/50 mL; COLCHICUM AUTUMNALE BULB 12 [hp_X]/50 mL; PROTORTONIA CACTI 631 mg/50 mL; SOLIDAGO VIRGAUREA FLOWERING TOP 2913 mg/50 mL; CAPSELLA BURSA-PASTORIS TOP 510 mg/50 mL
INACTIVE INGREDIENTS: WATER; ALCOHOL

RENELIX™

ACTIVE INGREDIENT

Ingredients:
Acidum benzoicum e resina | 4X
Acidum nitricum | 6X
Apis mellifica | 4X
Berberis vulgaris | 3X
Colchicum autumnale | 12X
Dactylopius coccus (Coccus cacti) | 12.62 mg/ml
Solidago virgaurea | 58.26 mg/ml
Capsella bursa pastoris (Thlaspi bursa pastoris) | 10.20 mg/ml

Selected ingredients prepared by spagyric processes.

INACTIVE INGREDIENT

Contains 25% alcohol by volume.

Indications

PURPOSE

Helps cleanse and detoxify the body. Application of this homeopathic remedy for the designated usage is exclusively based on homeopathic experience. With severe forms of this disease, a clinically proven therapy is indicated.

Dosage

Unless otherwise prescribed, adults take 15-20 drops, 3 times per day. For pediatric dosages, consult your practitioner.

Warning

ASK DOCTOR

If symptoms persist, contact a licensed practitioner. If you have known sensitivity to any of the ingredients, please consult your licensed practitioner before use. If you are pregnant or nursing a baby, seek the advice of a health care professional before use.

Keep out of the reach of children.

STORAGE AND HANDLING

Protect from light and heat.

Tamper Evident

Do not use this product if tamper evident strip is broken or removed from base of cap.

QUESTIONS

To report adverse events, contact BioResource at 321B Blodgett Street, Cotati, CA 94931

Distributed by:
BioResource Inc.
Cotati, CA 94931

Manufactured by:
PEKANA® GmbH
D-88353 Kisslegg

PRINCIPAL DISPLAY PANEL - 100 ml Bottle Box

RENELIX™

Oral Drops

Homeopathic Medicine

Helps cleanse and
detoxify the body

3.34 FL OZ
(100 ml)

PEKANA®